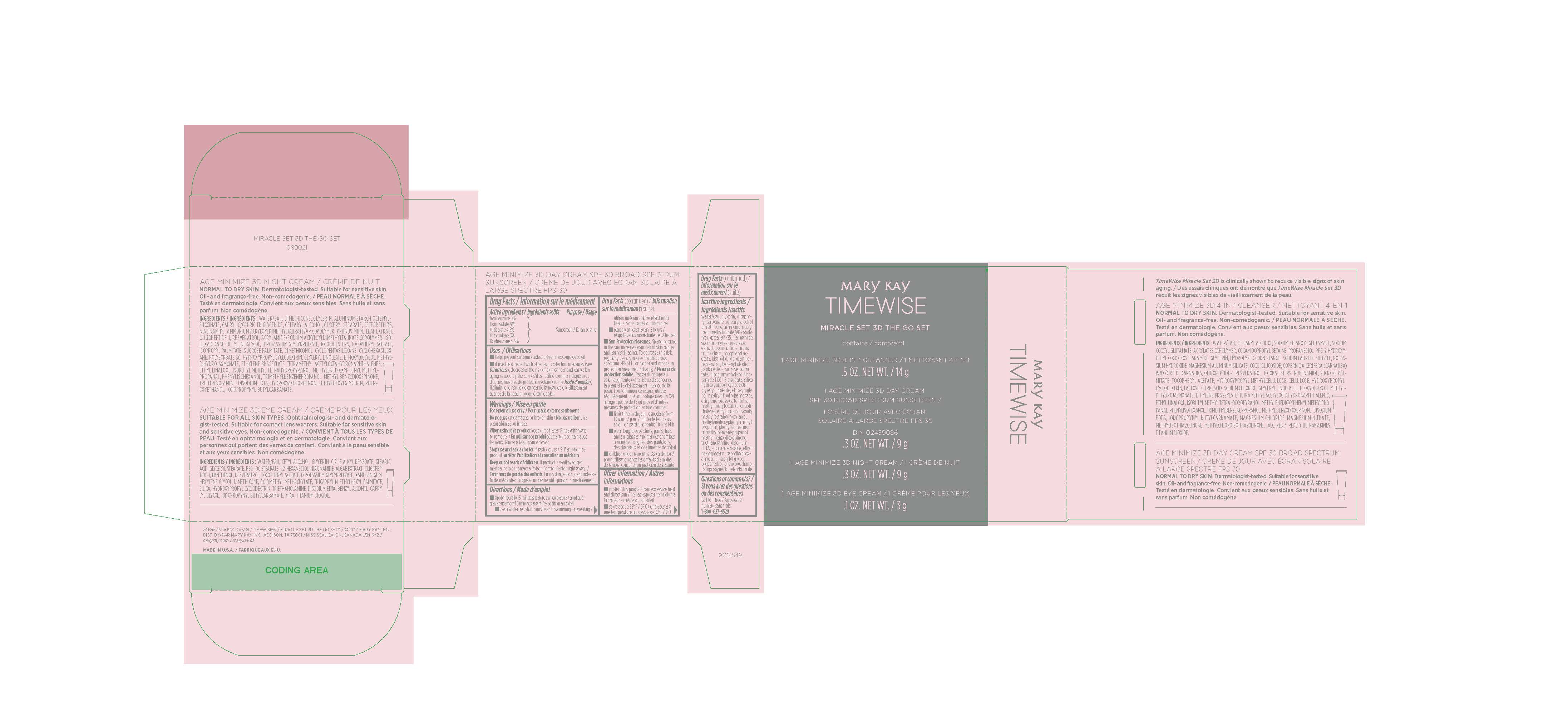 DRUG LABEL: Mary Kay TimeWise Miracle Set 3D The Go Set (Normal to Dry Skin)
NDC: 51531-9021 | Form: KIT | Route: TOPICAL
Manufacturer: Mary Kay Inc.
Category: otc | Type: HUMAN OTC DRUG LABEL
Date: 20241217

ACTIVE INGREDIENTS: AVOBENZONE 3 g/100 g; HOMOSALATE 9 g/100 g; OCTISALATE 4.5 g/100 g; OCTOCRYLENE 3 g/100 g; OXYBENZONE 4.5 g/100 g
INACTIVE INGREDIENTS: WATER; GLYCERIN; DICAPRYLYL CARBONATE; CETOSTEARYL ALCOHOL; DIMETHICONE; ETHYLENE BRASSYLATE; AMMONIUM ACRYLOYLDIMETHYLTAURATE/VP COPOLYMER; CETEARETH-25; NIACINAMIDE; SACCHAROMYCES CEREVISIAE; PRICKLY PEAR FRUIT; .ALPHA.-TOCOPHEROL ACETATE; LEVOMENOL; RESVERATROL; DOCOSANOL; JOJOBA OIL, RANDOMIZED; SUCROSE PALMITATE; DISODIUM ETHYLENE DICOCAMIDE PEG-15 DISULFATE; SILICON DIOXIDE; HYDROXYPROPYL .ALPHA.-CYCLODEXTRIN; GLYCERYL MONOLINOLEATE; DIETHYLENE GLYCOL MONOETHYL ETHER; METHYL DIHYDROJASMONATE (SYNTHETIC); TETRAMETHYL ACETYLOCTAHYDRONAPHTHALENES; ETHYL LINALOOL; 2-ISOBUTYL-4-METHYLTETRAHYDROPYRAN-4-OL; 3-(3,4-METHYLENEDIOXYPHENYL)-2-METHYLPROPANAL; PHENYLISOHEXANOL; TRIMETHYLBENZENEPROPANOL; METHYL BENZODIOXEPINONE; TROLAMINE; EDETATE DISODIUM; SODIUM BENZOATE; ETHYLHEXYLGLYCERIN; CAPRYLHYDROXAMIC ACID; CAPRYLYL GLYCOL; PROPANEDIOL; PHENOXYETHANOL; IODOPROPYNYL BUTYLCARBAMATE

Mary Kay
TimeWise Miracle Set 3D The Go Set (Normal/Dry)

Ingredients

WATER, CETEARYL ALCOHOL, SODIUM STEAROYL GLUTAMATE, SODIUM COCOYL GLUTAMATE, ACRYLATES COPOLYMER, COCAMIDOPROPYL BETAINE, PROPANEDIOL, PPG-2 HYDROXYETHYL COCO/ISOSTEARAMIDE, GLYCERIN, HYDROLYZED CORN STARCH, SODIUM LAURETH SULFATE, POTASSIUM HYDROXIDE, MAGNESIUM ALUMINUM SILICATE, COCO-GLUCOSIDE, COPERNICIA CERIFERA (CARNAUBA) WAX/CIRE DE CARNAUBA, OLIGOPEPTIDE-1, RESVERATROL, JOJOBA ESTERS, NIACINAMIDE, SUCROSE PALMITATE, TOCOPHERYL ACETATE, HYDROXYPROPYL METHYLCELLULOSE, CELLULOSE, HYDROXYPROPYL CYCLODEXTRIN, LACTOSE, CITRIC ACID, SODIUM CHLORIDE, GLYCERYL LINOLEATE, ETHOXYDIGLYCOL, METHYLDIHYDROJASMONATE, ETHYLENE BRASSYLATE, TETRAMETHYL ACETYLOCTAHYDRONAPHTHALENES, ETHYL LINALOOL, ISOBUTYL METHYL TETRAHYDROPYRANOL, METHYLENEDIOXYPHENYL METHYLPROPANAL, PHENYLISOHEXANOL, TRIMETHYLBENZENEPROPANOL, METHYL BENZODIOXEPINONE, DISODIUM EDTA, IODOPROPYNYL BUTYLCARBAMATE, MAGNESIUM CHLORIDE, MAGNESIUM NITRATE, METHYLISOTHIAZOLINONE, METHYLCHLOROISOTHIAZOLINONE, TALC, RED 7, RED 30, ULTRAMARINES, TITANIUM DIOXIDE.

Age Minimize 3D Day Cream SPF 30 Broad-Spectrum Sunscreen

Drug Facts

Active ingredients

Avobenzone 3%

Homosalate 9%

Octisalate 4.5%

Octocrylene 3%

Oxybenzone 4.5%

Purpose

Sunscreen

Uses

- helps prevent sunburn
- if used as directed with other sun protection measures (see Directions), decreases the risk of skin cancer and early skin aging caused by the sun

Warnings

For external use only

Do not use

on damaged or broken skin

When using this product

keep out of eyes. Rinse with water to remove.

Stop use and ask a doctor

if rash occurs

Keep out of reach of children.

If product is swallowed, get medical help or contact a Poison Control Center right away.

Directions

- apply liberally 15 minutes before sun exposure
- use a water resistant sunscreen if swimming or sweating
- reapply at least every 2 hours
- Sun Protection Measures. Spending time in the sun increases your risk of skin cancer and early skin aging. To decrease this
  risk, regularly use a sunscreen with a broad spectrum SPF of 15 or higher and other sun protection measures including:
- limit time in the sun, especially from 10 a.m. - 2 p.m.
- wear long-sleeve shirts, pants, hats, and sunglasses
- children under 6 months: Ask a doctor

Other information

- protect this product from excessive heat and direct sun
- store above 32° F / 0° C

Inactive ingredients

water, glycerin, dicaprylyl carbonate, cetearyl alcohol, dimethicone, ammonium acryloyldimethyltaurate/VP copolymer, ceteareth-25, niacinamide, saccharomyces cerevisiae extract, opuntia ficus-indica fruit extract, tocopheryl acetate, bisabolol, oligopeptide-1, resveratrol, behenyl alcohol, jojoba esters, sucrose palmitate, disodium ethylene dicocamide PEG-15 disulfate, silica, hydroxypropyl cyclodextrin, glyceryl linoleate, ethoxydiglycol, methyldihydrojasmonate, ethylene brassylate, tetramethyl acetyloctahydronaphthalenes, ethyl linalool, isobutyl methyl tetrahydropyranol, methylenedioxyphenyl methylpropanal, phenylisohexanol, trimethylbenzenepropanol, methyl benzodioxepinone, triethanolamine, disodium EDTA, sodium benzoate, ethylhexylglycerin, caprylhydroxamic acid, caprylyl glycol, propanediol, phenoxyethanol, iodopropynyl butylcarbamate.

Questions or comments?

Call toll-free 1-800-627-9529

INGREDIENTS:

WATER, DIMETHICONE, GLYCERIN, ALUMINUM STARCH OCTENYLSUCCINATE, CAPRYLIC/CAPRIC TRIGLYCERIDE, CETEARYL ALCOHOL, GLYCERYL STEARATE, CETEARETH-33, NIACINAMIDE, AMMONIUM ACRYLOYLDIMETHYLTAURATE/VP COPOLYMER, PRUNUS MUME LEAF EXTRACT, OLIGOPEPTIDE-1, RESVERATROL, ACRYLAMIDE/SODIUM ACRYLOYLDIMETHYLTAURATE COPOLYMER, ISOHEXADECANE, BUTYLENE GLYCOL, DIPOTASSIUM GLYCYRRHIZATE, JOJOBA ESTERS, TOCOPHERYL ACETATE, ISOPROPYL PALMITATE, SUCROSE PALMITATE, DIMETHICONOL, POLYSORBATE 80, HYDROXYPROPYL CYCLODEXTRIN, GLYCERYL LINOLEATE, ETHOXYDIGLYCOL, METHYLDIHYDROJASMONATE, ETHYLENE BRASSYLATE, TETRAMETHYL ACETYLOCTAHYDRONAPHTHALENES, ETHYL LINALOOL, ISOBUTYL METHYL TETRAHYDROPYRANOL, METHYLENEDIOXYPHENYL METHYLPROPANAL, PHENYLISOHEXANOL, TRIMETHYLBENZENEPROPANOL, METHYL BENZODIOXEPINONE, TRIETHANOLAMINE, DISODIUM EDTA, HYDROXYACETOPHENONE, ETHYLHEXYLGLYCERIN, PHENOXYETHANOL, IODOPROPYNYL BUTYLCARBAMATE.

INGREDIENTS:

WATER/EAU, CETYL ALCOHOL, GLYCERIN, C12-15 ALKYL BENZOATE, STEARIC ACID, GLYCERYL STEARATE, PEG-100 STEARATE, 1,2-HEXANEDIOL, NIACINAMIDE, ALGAE EXTRACT, OLIGOPEPTIDE-1, PANTHENOL, RESVERATROL, TOCOPHERYL ACETATE, DIPOTASSIUM GLYCYRRHIZATE, XANTHAN GUM, HEXYLENE GLYCOL, DIMETHICONE, POLYMETHYL METHACRYLATE, TRICAPRYLIN, ETHYLHEXYL PALMITATE, SILICA, HYDROXYPROPYL CYCLODEXTRIN, TRIETHANOLAMINE, DISODIUM EDTA, BENZYL ALCOHOL, CAPRYLYL GLYCOL, IODOPROPYNYL BUTYLCARBAMATE, MICA, TITANIUM DIOXIDE.

Principal Display Panel - The Go Set Normal/Dry carton

Mary Kay TimeWise Miracle Set 3D The Go Set

contains:

1 Age Minimize 3D 4-in-1 Cleanser .5 OZ. NET WT. / 14 g

1 Age Minimize 3D Day Cream SPF 30 Broad-Spectrum Sunscreen .3 OZ. NET WT. / 9 g

1 Age Minimize 3D Night Cream .3 OZ. NET WT. / 9 g

1 Age Minimize Eye Cream .1 OZ. NET WT. / 3 g